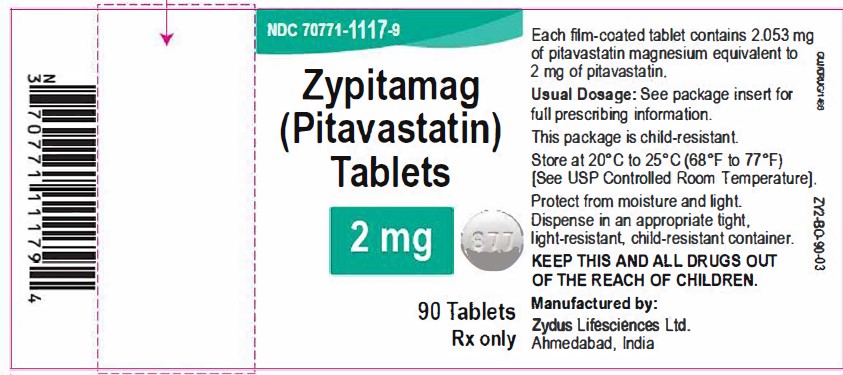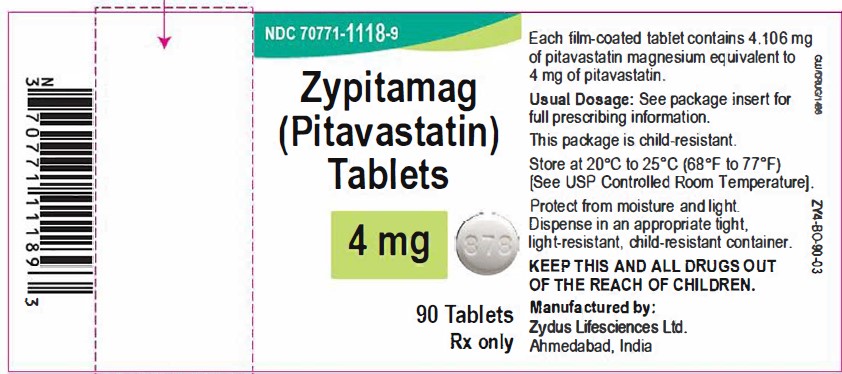 DRUG LABEL: ZYPITAMAG
NDC: 70771-1117 | Form: TABLET, FILM COATED
Manufacturer: Zydus Lifesciences Limited
Category: prescription | Type: HUMAN PRESCRIPTION DRUG LABEL
Date: 20240814

ACTIVE INGREDIENTS: PITAVASTATIN 2 mg/1 1
INACTIVE INGREDIENTS: CALCIUM CARBONATE; CROSPOVIDONE; HYPROMELLOSE, UNSPECIFIED; LACTOSE MONOHYDRATE; MAGNESIUM STEARATE; POLYETHYLENE GLYCOL, UNSPECIFIED; SODIUM CARBONATE; TALC; TITANIUM DIOXIDE

ZYPITAMAG (pitavastatin) tablets

PACKAGE LABEL.PRINCIPAL DISPLAY PANEL

NDC 70771-1117-9

Zypitamag (Pitavastatin) Tablets, 2 mg

90 Tablets

Rx only

NDC 70771-1118-9

Zypitamag (Pitavastatin) Tablets, 4 mg

90 Tablets

Rx only